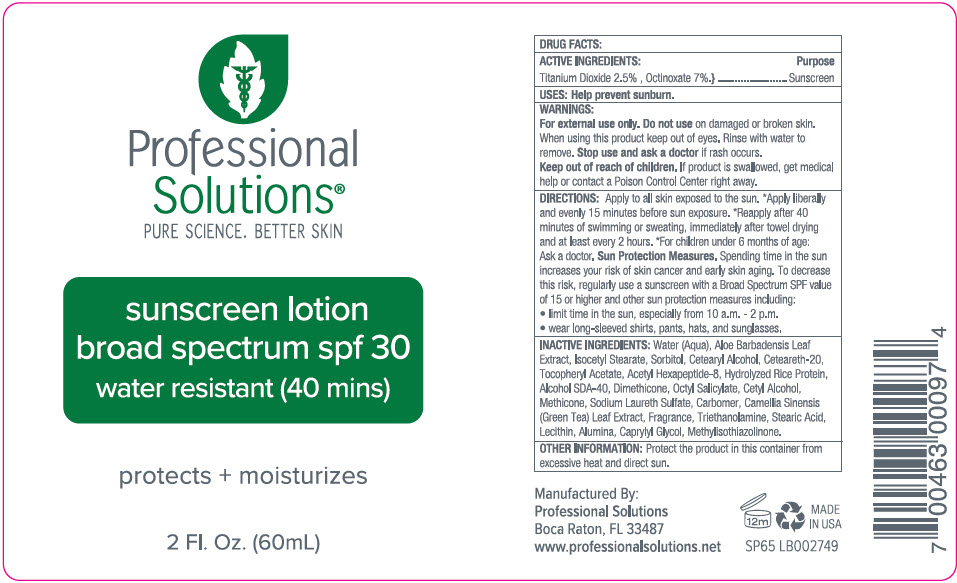 DRUG LABEL: Professional Solutions Suncreen SPF 30
NDC: 66163-6500 | Form: LOTION
Manufacturer: Cosmetic Solutions LLC
Category: otc | Type: HUMAN OTC DRUG LABEL
Date: 20190925

ACTIVE INGREDIENTS: OCTINOXATE 70 mg/1 mL; TITANIUM DIOXIDE 25 mg/1 mL
INACTIVE INGREDIENTS: Water; Aloe Vera Leaf; Isocetyl Stearate; Sorbitol; Cetostearyl Alcohol; Polyoxyl 20 Cetostearyl Ether; .Alpha.-Tocopherol Acetate; Acetyl Hexapeptide-8; Dimethicone; Octisalate; Cetyl Alcohol; Methicone (20 Cst); Sodium Laureth-3 Sulfate; Carboxypolymethylene; Green Tea Leaf; Trolamine; Stearic Acid; Triethoxycaprylylsilane; Aluminum Oxide; Caprylyl Glycol; Methylisothiazolinone

Professional Solutions® Suncreen SPF 30

DRUG FACTS:

ACTIVE INGREDIENTS

Octinoxate 7%

Titanium Dioxide 2.5%

PURPOSE

Sunscreen

USES

Helps prevent sunburn.

WARNINGS

For external use only. Do not use on damaged or broken skin. When using this product keep out of eyes. Rinse with water to remove.Stop use and ask a doctor if rash occurs.

Keep out of reach of children. If product is swallowed, get medical help or contact a Poison Control Center right away.

DIRECTIONS

Apply generously until desired coverage is achieved. If exposed to sun, reapply every 2 hours. If swimming or sweating, use water resistant sunscreen.

Sun Protection Measures.

Spending time in the sun increases your risk of skin cancer and early skin aging.To decrease this risk, regularly use a sunscreen with a Broad Spectrum SPF value of 15 or higher and other sun protection measures including:

- limit time in the sun, especially from 10 a.m. - 2 p.m.
- wear long-sleeved shirts, pants, hats, and sunglasses.

INACTIVE INGREDIENTS

Water (Aqua), Aloe Barbadensis Leaf Extract, Isocetyl Stearate, Sorbitol, Cetearyl Alcohol, Ceteareth-20, Tocopheryl Acetate, Acetyl Hexapeptide-8, Hydrolyzed Rice Protein, Alcohol SDA-40, Dimethicone, Octyl Salicylate, Cetyl Alcohol, Sodium Laureth Sulfate, Carbomer, Camellia Sinensis (Green Tea) Leaf Extract, Fragrance, Triethanolamine, Triethoxycaprylylsilane, Lecithin, Caprylyl Glycol, Methylisothiazolinone.

OTHER INFORMATION

Protect the product in this container from excessive heat and direct sun.

Manufactured By:
Professional Solutions
Boca Raton, FL 33487

PRINCIPAL DISPLAY PANEL - 60 mL Bottle Label

Professional
Solutions®
PURE SCIENCE. BETTER SKIN

sunscreen lotion
broad spectrum spf 30
water resistant (40 mins)

protects + moisturizes

2 Fl. Oz. (60mL)